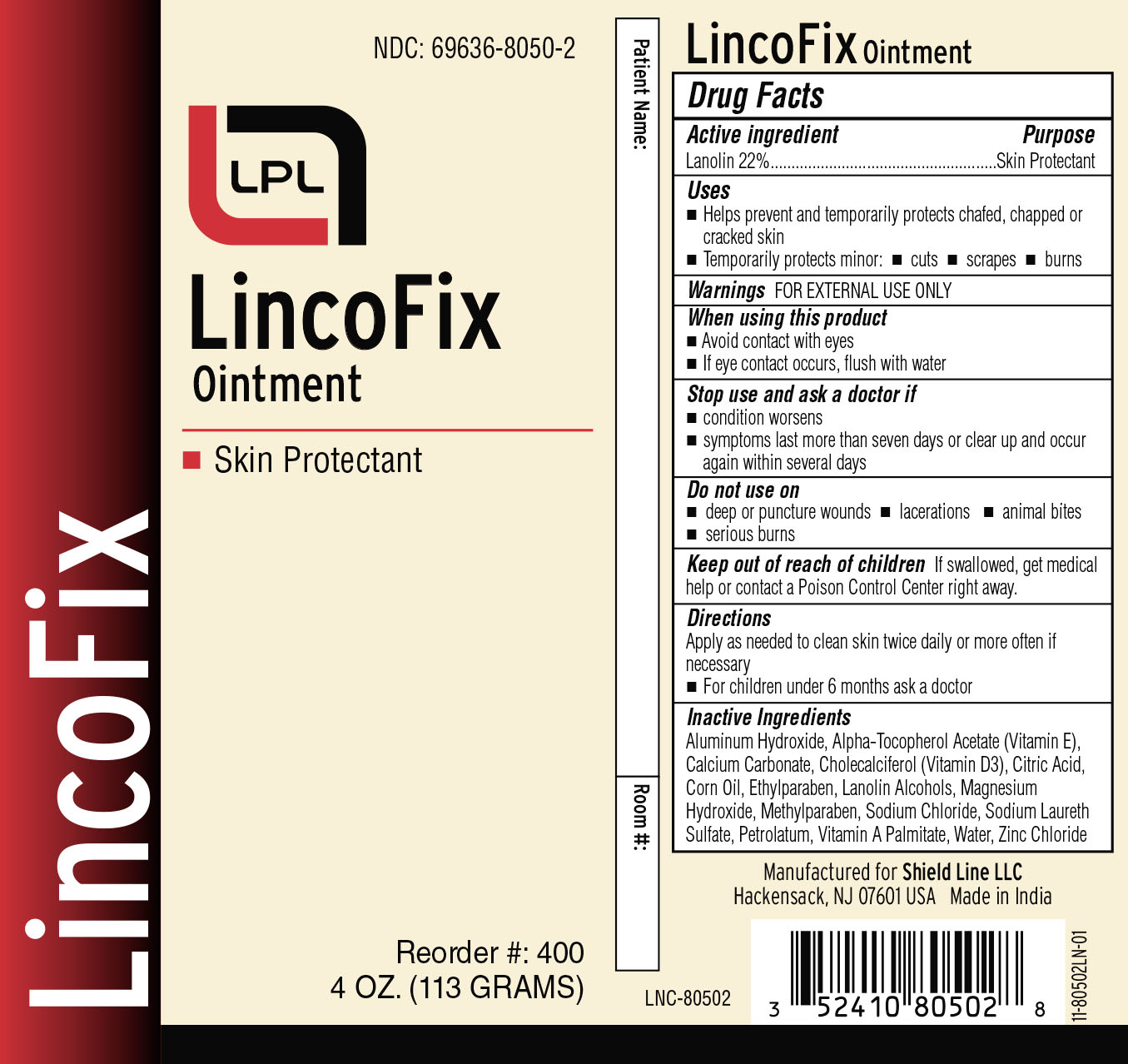 DRUG LABEL: LincoFix
NDC: 69636-8050 | Form: OINTMENT
Manufacturer: Lincoln Pharmaceuticals Ltd.
Category: otc | Type: HUMAN OTC DRUG LABEL
Date: 20161005

ACTIVE INGREDIENTS: LANOLIN 22 g/100 g
INACTIVE INGREDIENTS: CORN OIL; ETHYLPARABEN; LANOLIN ALCOHOLS; ALUMINUM HYDROXIDE; CALCIUM CARBONATE; METHYLPARABEN; WATER; ALPHA-TOCOPHEROL ACETATE; CHOLECALCIFEROL; CITRIC ACID MONOHYDRATE; MAGNESIUM HYDROXIDE; SODIUM CHLORIDE; SODIUM LAURETH SULFATE; PETROLATUM; VITAMIN A PALMITATE; ZINC CHLORIDE

Active Ingredient

Lanolin 22%

Purpose

Skin Protectant

Uses

- Helps prevent and temporarily protects chafed, chapped or cracked skin
- Temporarily protects minor cuts, scrapes, burns

Warnings

FOR EXTERNAL USE ONLY

When using this product

- Avoid contact with eyes
- If contact occurs, flush with water

Stop use and ask a doctor if

- condition worsens
- symptoms last more than seven days or clear up and occur again within seven days

Do not use on

- deep or puncture wounds
- lacerations
- animal bites
- serious burns

Keep out of reach of children

If swallowed, get medical help or contact a Poison Control Center right away

Directions

Apply as needed to clean skin twice daily or more often if necessary

- For Children under 6 months ask a doctor

Inactive Ingredients

Aluminium Hydroxide, Alpha Tocopherol Acetate(Vitamin E), Calcium carbonate, Cholecalciferol (Vitamin D3), Citric Acid,Corn Oil, Ethylparaben, Lanolin, Magnesium Hydroxide, Methylparaben, Sodium Chloride, Sodium laureth Sulfate, Petrolatum, Vitamin A Palmitate, Water, Zinc Chloride